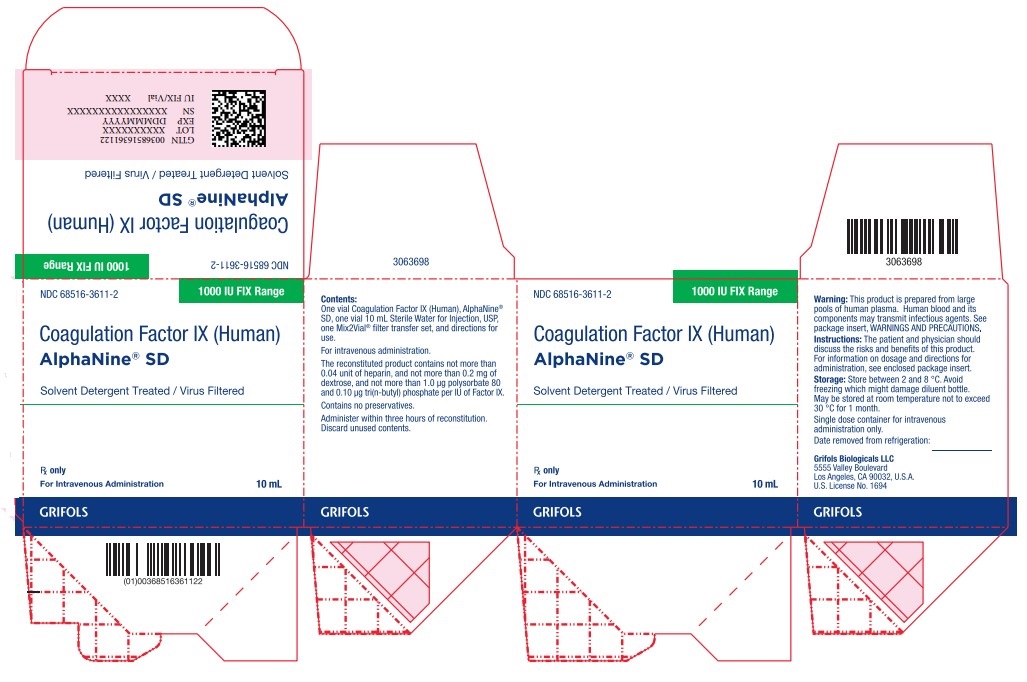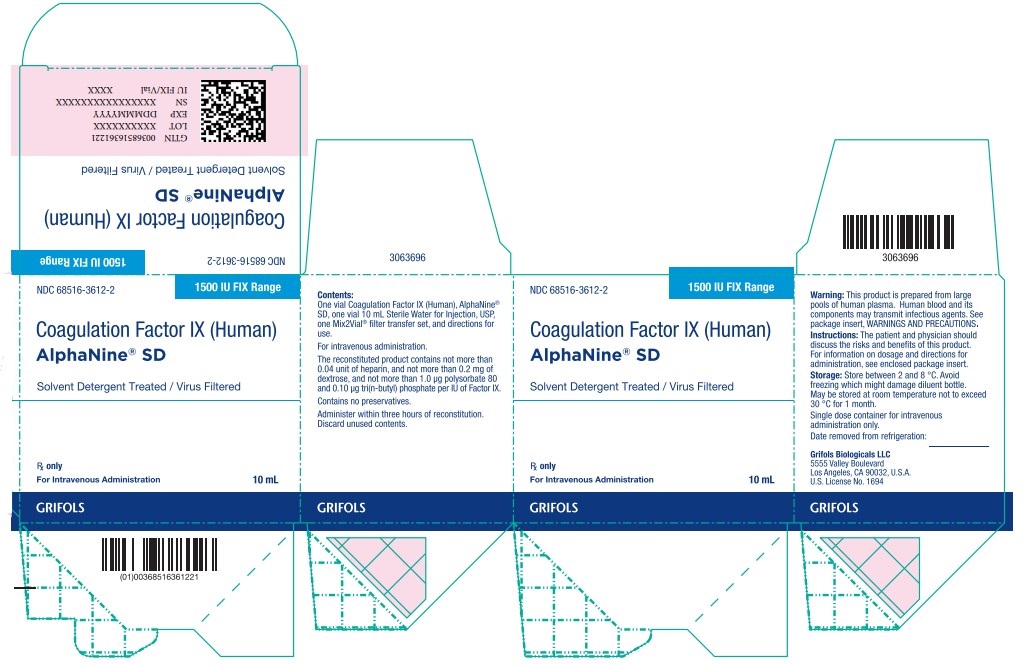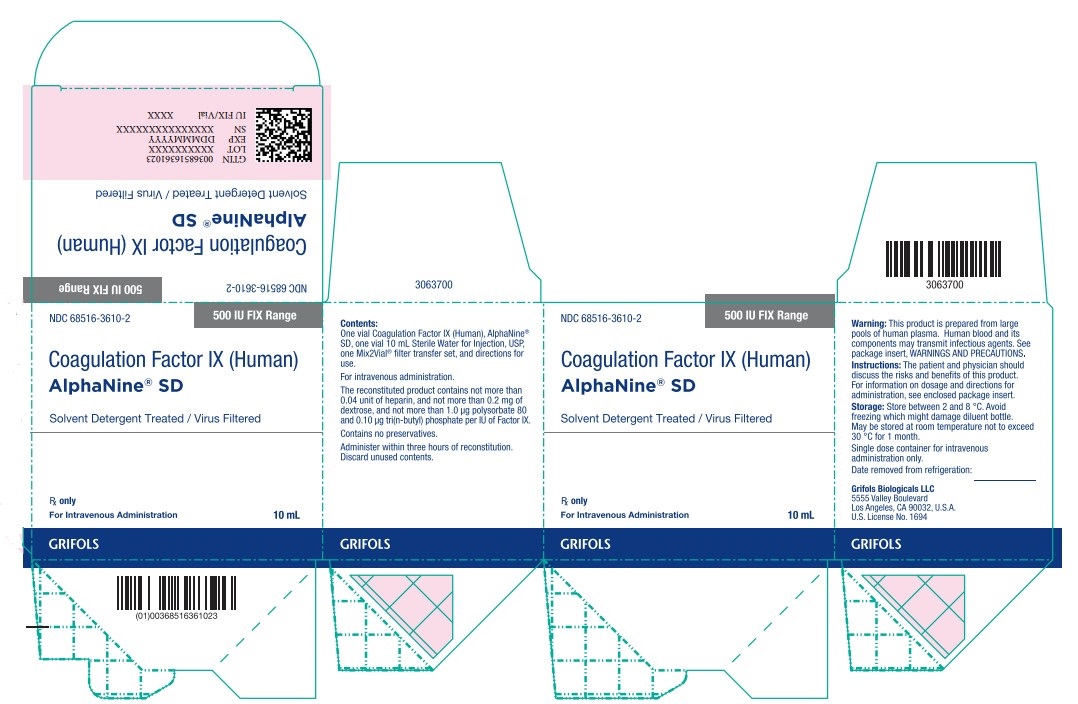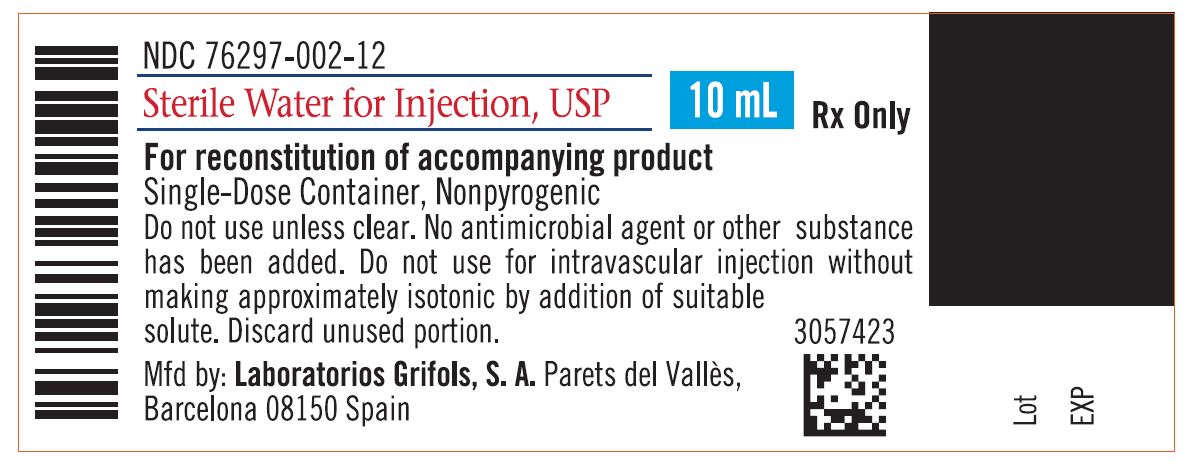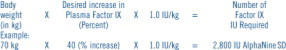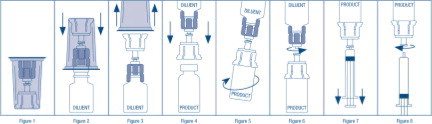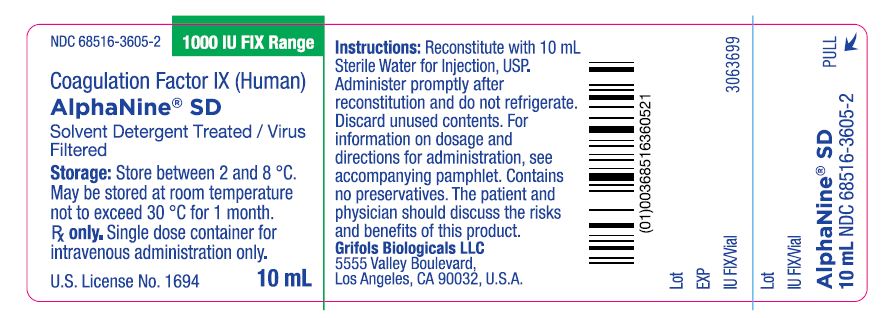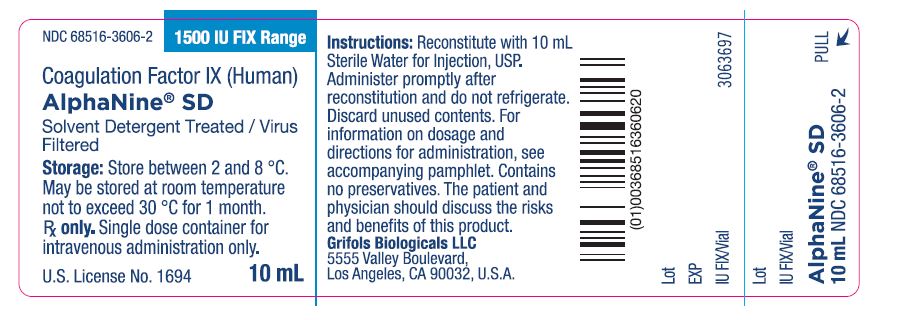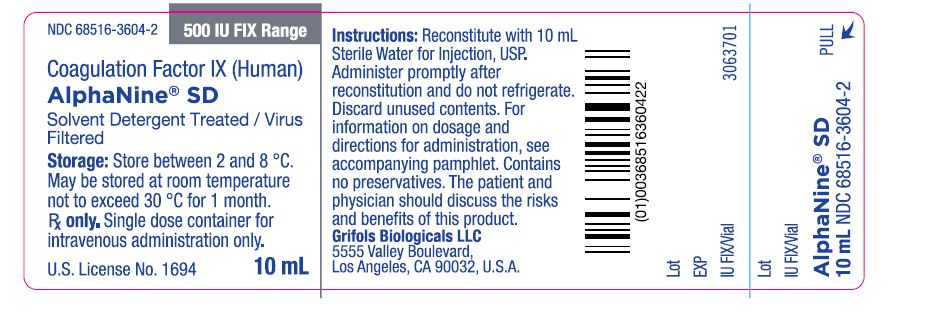 DRUG LABEL: AlphaNine 
NDC: 68516-3607 | Form: KIT | Route: INTRAVENOUS
Manufacturer: GRIFOLS USA, LLC
Category: other | Type: PLASMA DERIVATIVE
Date: 20250527

ACTIVE INGREDIENTS: COAGULATION FACTOR IX HUMAN 500 [iU]/10 mL; water 1 mL/1 mL
INACTIVE INGREDIENTS: dextrose; heparin; sodium chloride; sodium citrate

Coagulation Factor IX (Human), AlphaNine® SD
Solvent Detergent Treated/Virus Filtered

DESCRIPTION

Coagulation Factor IX (Human), AlphaNine® SD, is a purified, solvent detergent treated, virus filtered preparation of Factor IX derived from human plasma.^1 It contains a minimum of 150 IU Factor IX/mg protein; levels of Factor VII (proconvertin), Factor II (prothrombin) and Factor X (Stuart-Prower Factor) which are below the limit of detection (less than 0.04 Factor VII unit, less than 0.05 Factor II unit, and less than 0.05 Factor X unit per IU Factor IX). AlphaNine SD is a sterile, lyophilized preparation intended for intravenous administration only. Each vial is a single dose container.

AlphaNine SD is labeled with the Factor IX potency expressed in International Units (IU). AlphaNine SD contains not more than (NMT) 0.04 unit of heparin, NMT 0.2 mg of dextrose, NMT 1.0 μg polysorbate 80 and NMT 0.10 μg tri(n-butyl) phosphate/IU of Factor IX. Contains no preservatives.

CLINICAL PHARMACOLOGY

AlphaNine SD is a purified formulation of Factor IX containing not less than 150 IU Factor IX activity/mg of total protein.^2 AlphaNine SD contains non-therapeutic levels of Factor II, Factor VII and Factor X.

Thrombogenicity of AlphaNine SD in animals is markedly lower than that of Factor IX Complex, Profilnine® Heat-Treated. Five lots of AlphaNine SD (three lots of non-virus filtered product and two lots of virus filtered product) failed to show any evidence of thrombogenicity when tested directly in the Wessler rabbit stasis model for thrombogenicity^3-6 at a dose of 200 IU Factor IX/kg body weight. When various lots of AlphaNine SD were further tested at doses between 300 and 650 IU Factor IX/kg, only 5 out of 40 animals (12.5%) showed evidence of thrombus formation (Wessler scores of +1, +2, +1, +1, +1 out of +4 maximum). In comparison, Factor IX Complex concentrate, Profilnine, was thrombogenic in 100% of the animals tested at a dose of 100 IU Factor IX/kg.

At a dose of 200 IU Factor IX/kg body weight in a porcine model, the heptane heat-treated formulation of this product (AlphaNine) showed little evidence of disseminated intravascular coagulation (DIC) following infusion.^7 This model exhibited no depletion of coagulation factors, a minimal increase in fibrin monomer (+1 in protamine test), a slight temporary decrease in platelet counts, and no evidence of intravascular coagulation upon gross autopsy.^8 In contrast, Harrison, et al., report that all Factor IX Complex concentrates studied in the same porcine model were thrombogenic at doses between 50 and 100 IU of Factor IX/kg animal weight.^9

A clinical evaluation of AlphaNine SD half-life and recovery characteristics was performed. A total of 18 patients with severe to moderate hemophilia B each received a single infusion of 40 to 50 IU Factor IX/kg body weight of AlphaNine SD. Following the administration of AlphaNine SD, the mean half-life of Factor IX observed was approximately 21 hours.^2 This half-life value was computed using the biphasic linear regression model recommended by the International Society of Thrombosis and Haemostasis.^10 The half-life obtained for the solvent detergent treated product is comparable to that of AlphaNine (approximately 19 hours) as well as the range of 18 to 36 hours reported for Factor IX Complex preparations.^11 The mean recovery observed in clinical trials was approximately 48% and was comparable to that of AlphaNine (approximately 51%).^2

A clinical trial was conducted using the heptane heat-treated product, AlphaNine, to evaluate the efficacy of the product in providing hemostatic protection during and after surgery in 13 patients with hemophilia B. The types of surgical procedures performed included bilateral knee replacement (1), total knee replacement with synovectomy (2), hip replacement (1), below the knee amputation (1), herniorrhaphy (2), hemorrhoidectomy (1), rhinoplasty (2), oral surgery (2) and Hickman catheter insertion with temporalis muscle transfer (1). Presurgery doses ranged from 30.1 to 65.0 IU Factor IX/kg; postsurgery replacement therapy doses ranged from approximately 9.4 to 52.0 IU Factor IX/kg. The number of postsurgery days of treatment ranged from 1 to 23; the number of postsurgery infusions ranged from 2 to 26. No bleeding episodes were reported and hemostasis was maintained during the course of postsurgery therapy. None of the hematologic parameters examined (hematocrit, partial thromboplastin time, prothrombin time, fibrinogen/fibrin degradation products, fibrin monomers, D-dimers and platelet counts) provided any evidence that AlphaNine possessed thrombogenic potential.^12

A randomized crossover study with 11 hemophilia B patients was conducted with the heptane heat-treated version of the product, AlphaNine, to determine whether an infusion of AlphaNine caused less activation of the hemostatic system than the Factor IX Complex concentrate preparation, Profilnine Heat-Treated. Each subject received a single infusion of either AlphaNine or Profilnine Heat-Treated for the treatment of a bleeding episode, at a dose of 50 IU Factor IX/kg body weight. Each subject received the other Factor IX concentrate for the treatment of a subsequent bleeding episode, separated by an interval of not less than 10 days. The level of prothrombin fragment 1+2 (F1+2) is a sensitive index of the cleavage of prothrombin by activated Factor X. The level of fibrinopeptide A (FPA) released into the plasma measures the activity of thrombin on fibrinogen in the formation of fibrin. Following infusion of Factor IX Complex, statistically significant increases in F1+2 and in FPA were detected at all monitored time points (15, 60, 90, 120 and 240 minutes postinfusion). The statistically significant elevation in these two hemostatic parameters indicates increased activation of the coagulation cascade. Administration of AlphaNine resulted in no increase in F1+2 at any monitored time points, and a statistically non-significant increase in FPA at 15, 60, and 90 minutes following infusion. Only at 120 and 240 minutes after infusion of AlphaNine were statistically significant increases in FPA levels detected. These results suggest that the infusion of a high purity factor IX, such as AlphaNine, may result in a lower level of activation of the coagulation cascade than does Factor IX Complex.^13

The ability of the manufacturing process to inactivate and eliminate virus from the Coagulation Factor IX (Human) products was evaluated at key stages in the process (see Table 1). Known amounts of different viruses were added to samples obtained prior to those steps most likely to reduce virus load (DEAE Chromatography, Solvent Detergent, Dual Affinity Chromatography and nanofiltration) in the AlphaNine and AlphaNine SD processes to determine the level of viral inactivation/elimination of these specific steps in the process.

Table 1
Process Step | Virus Reduction (log10)
Process Step | Sindbis | VSV | HIV-1 | HIV-2 | Parvo** | EMC | Reo | HAV
DEAE Chromatography | 1.4 | NT | NT | NT | 1.5* | NT | NT | NT
Solvent- Detergent | NLT 5.3 | NLT 4.9 | NLT 12.2 | 6.0 | NT | NT | NT | NT
Dual Affinity Chromatography | 4.7 | NT | NT | NT | 2.2* | NT | NT | NT
Nanofiltration | NT | NT | NT | NT | 3.6 | 3.4 | 4.1 | ≥ 4.4
**Porcine NT=Not tested NLT=Not less than *Lower 95% confidence interval

The retrovirus known as human immunodeficiency virus (HIV) has been identified as a causative agent of Acquired Immunodeficiency Syndrome (AIDS) and has been shown to be transmissible via blood or blood products. The solvent detergent process used in the manufacture of AlphaNine SD, was shown to inactivate greater than 12.2 logs of HIV-1 when the retrovirus was intentionally added to product samples under laboratory evaluation (as measured by virus antigen capture and reverse transcriptase assays). In addition, this process was shown to inactivate 6 logs of HIV-2 (as measured by reverse transcriptase assays) when the retrovirus was intentionally added to product samples.^2 In an on going efficacy and safety study of 26 patients, no subjects tested positive for HIV or viral hepatitis in relation to the investigation drug.^2

In order to assess the ability of the solvent detergent treatment process to inactivate other viruses such as hepatitis B and C virus, the inactivation of the model viruses, Sindbis virus, a model virus for hepatitis C virus, and vesicular stomatitis virus (VSV), a model RNA virus for lipid enveloped viruses, by solvent detergent treatment was studied. Prior to solvent detergent treatment, samples were inoculated with a titer of either Sindbis or VSV. The results demonstrated that a minimum of 5.3 logs of Sindbis and a minimum of 4.9 logs of VSV were inactivated after 180 minutes of incubation with solvent detergent (when compared to an untreated control). It should be noted that the incubation time in the actual AlphaNine SD process is twice (360 minutes total) that used in the model virus studies.

The ability of the AlphaNine SD process to eliminate virus, by physically partitioning virus from product, was evaluated at key stages of the manufacturing process. Studies were performed using a lipid-enveloped model virus (Sindbis) and non-lipid model viruses (porcine parvovirus, encephalomyocarditis virus, and reovirus). Known amounts of these viruses were added to samples obtained from the AlphaNine SD process. The amount of virus removed at each subsequent purification step was then determined by plaque assay.

Addition of Sindbis or porcine parvovirus prior to Factor IX Complex adsorption by DEAE chromatography showed this step to eliminate 1.4 logs of Sindbis and 1.5 logs (95% confidence interval: 1.51-2.33) of added porcine parvovirus. When Sindbis or parvovirus was introduced into the process after the barium citrate precipitation step of the AlphaNine SD process, the subsequent dual affinity chromatography step was found to eliminate 4.7 logs of Sindbis and 2.2 logs (95% confidence interval: 2.25-2.75) of added parvovirus. When parvovirus, encephalomyocarditis virus (EMC), or Reovirus was introduced into the process after the dual affinity chromatography step, the subsequent nanofiltration step of the AlphaNine SD process was found to eliminate 3.6 logs of parvovirus, 3.4 logs of EMC and 4.1 logs of added Reovirus. The studies mentioned above indicate that the manufacturing process of AlphaNine SD is capable of reducing viruses by approximately 6 logs, in addition to virus reduction achieved by the solvent detergent process.^14 In another study, the nanofiltration step removed ≥ 4.4 logs of hepatitis A virus (HAV), a non-lipid enveloped virus. Table 1 summarizes the reduction factors obtained for each virus when individual steps in the manufacturing process for AlphaNine SD were validated for virus removal/inactivation.

INDICATIONS AND USAGE

AlphaNine SD is indicated for the prevention and control of bleeding in patients with Factor IX deficiency due to hemophilia B. AlphaNine SD contains low, non-therapeutic levels of Factors II, VII, and X, and, therefore, is not indicated for the treatment of Factor II, VII or X deficiencies. This product is also not indicated for the reversal of coumarin anticoagulant-induced hemorrhage, nor in the treatment of hemophilia A patients with inhibitors to Factor VIII.

CONTRAINDICATIONS

None known.

WARNINGS

Because Coagulation Factor IX (Human), AlphaNine SD is made from pooled human plasma, it may carry a risk of transmitting infectious agents, e.g., viruses, and theoretically, the Creutzfeldt-Jakob disease (CJD) agent. Stringent procedures designed to reduce the risk of adventitious agent transmission have been employed in the manufacture of this product, from the screening of plasma donors and the collection and testing of plasma to the application of viral elimination/reduction steps such as column chromatography, solvent detergent treatment and nanofiltration in the manufacturing process. Despite these measures, such product can potentially transmit disease, therefore the risk of infectious agents cannot be totally eliminated. The physician should weigh the risks and benefits of the use of this product and should discuss these with the patient.

Individuals who receive infusions of blood or plasma products may develop signs and/or symptoms of some viral infections. Scientific opinion encourages hepatitis B and hepatitis A vaccinations at birth or diagnosis for patients with hemophilia.

Incidences of thrombosis or disseminated intravascular coagulation (DIC), have been reported following administration of Factor IX Complex concentrates which contain high amounts of Factor II, VII and X.

Following administration of Coagulation Factor IX (Human), AlphaNine SD in surgery patients and individuals with known liver disease, the physician should closely observe the patient for signs or symptoms of potential disseminated intravascular coagulation (DIC). Continued administration of the product should be left to the discretion of the physician.

Allergic type hypersensitivity reactions, including anaphylaxis, have been reported for all factor IX products. Frequently these events have occurred in close temporal association with the development of factor IX inhibitors. Patients should be informed of the early symptoms and signs of hypersensitivity reactions, including hives, generalized urticaria, angioedema, chest tightness, dyspnea, wheezing, faintness, hypotension, tachycardia and anaphylaxis. Patients should be advised to discontinue use of the product and contact physician and/or seek immediate emergency care, depending on the severity of the reactions, if any of these symptoms occur.

Nephrotic syndrome has been reported following attempted immune tolerance induction with factor IX products in Hemophilia B patients with factor IX inhibitors and a history of severe allergic reactions to Factor IX. The safety and efficacy of using AlphaNine SD in attempted immune tolerance induction has not been established.

In Previously Untreated Patients (PUPs), it is possible that anaphylaxis may occur after a median exposure of eleven (11) days.^15 It is recommended that these patients are monitored closely between the tenth and twentieth exposure day.

PRECAUTIONS

General

In order to minimize the possibility of thrombogenic complications, dosing guidelines should be strictly followed. Refer to “Dosage and Administration” section for recommended amount of product to be administered.

AlphaNine SD should not be administered at a rate exceeding 10 mL/minute. Rapid administration may result in vasomotor reactions.

Nursing personnel and others who administer this material should exercise appropriate caution in handling due to the risk of exposure to viral infection.

Discard any unused contents into the appropriate safety container. Discard administration equipment after single use into the appropriate safety container. Do not resterilize components.

Information for Patients

Patients should be informed of the early symptoms and signs of hypersensitivity reaction, including hives, generalized urticaria, chest tightness, dyspnea, wheezing, faintness, hypotension, and anaphylaxis. Patients should be advised to discontinue use of the product and contact their physician and/or seek immediate emergency care, depending on the severity of the reaction, if these symptoms occur.

Some viruses, such as parvovirus B19 or hepatitis A, are particularly difficult to remove or inactivate at this time. Parvovirus B19 may most seriously affect sero-negative pregnant women, or immunocompromised individuals. The majority of parvovirus B19 and hepatitis A infections are acquired by environmental (natural) sources.

Preliminary information suggests a relationship may exist between the presence of major deletion mutations in the Factor IX gene and an increased risk of inhibitor formation and of acute hypersensitivity reactions. Patients known to have major deletion mutations of the Factor IX gene should be observed closely for signs and symptoms of acute hypersensitivity reactions, particularly during the early phases of initial exposure to product.

Pregnancy

Animal reproduction studies have not been conducted with AlphaNine SD. It is also not known whether AlphaNine SD can cause fetal harm when administered to a pregnant woman or can affect reproduction capacity. AlphaNine SD should be given to a pregnant woman only if clearly indicated.

Pediatric Use

Clinical trials for safety and effectiveness in pediatric patients 16 years of age and younger have not been conducted. Across a well controlled half-life and recovery clinical trial in patients previously treated with Factor IX concentrates of Hemophilia B, the three pediatric patients receiving AlphaNine SD (solvent detergent treated) responded similarly when compared with 15 adult patients.^2 In an ongoing safety and efficacy clinical trial in patients not previously treated with Factor IX concentrates for Hemophilia B, 21 pediatric patients received AlphaNine SD (solvent detergent treated) responded similarly when compared with the five adult patients above the age of 16 years. Adverse events were similar in this group compared to the patients above the age of 16 years. Anecdotal evaluation of the results indicates no safety and efficacy differences between pediatric and adult populations.

ADVERSE REACTIONS

The administration of plasma preparations may cause allergic reactions, mild chills, nausea or stinging at the infusion site. For most reactive individuals, slowing the infusion rate relieves the symptoms. For those highly reactive individuals, a different lot may be satisfactory.

Adverse reactions, characterized by either thrombosis or disseminated intravascular coagulation (DIC), have been reported following administration of Factor IX Complex concentrates. Patients who receive Coagulation Factor IX (Human), AlphaNine SD, following operation, or those with known liver disease, should be kept under close observation for potential signs or symptoms of intravascular coagulation. Continued administration should be left to the discretion of the physician.

In the clinical study that compared the in vivo half-life and recovery of AlphaNine SD and HT products, no adverse events were associated with 18 infusions of AlphaNine SD administered to 18 individuals with severe to moderate hemophilia B.^2 Short term safety of the earlier version of this product, AlphaNine, was demonstrated by an absence of adverse events after 225 infusions of this product were received by 31 patients participating in three clinical trials. In the clinical trial to evaluate efficacy of AlphaNine in providing hemostatic protection during and after surgery, 13 patients received a total of 370,655 IU of AlphaNine. In 208 total infusions, each patient received approximately 15,000 IU (range 3,295 to 52,200 IU Factor IX) in an average of 16 infusions (range 2 to 26 infusions). Results from this study showed no bleeding episodes during the course of postsurgery therapy. There was no hematological evidence (measured by hematocrit, partial thromboplastin time, prothrombin time, fibrinogen/fibrin degradation products, fibrin monomers, D-dimers and platelet counts) of thrombogenicity.^12

To report SUSPECTED ADVERSE REACTIONS, contact Grifols at 1-888-GRIFOLS (1-888-474-3657) or FDA at 1-800-FDA-1088 or www.fda.gov/medwatch.

DOSAGE AND ADMINISTRATION

For adult usage:

AlphaNine SD should be administered intravenously promptly following reconstitution. Administration of AlphaNine SD within three hours after reconstitution is recommended to avoid the potential ill effect of any inadvertent bacterial contamination occurring during reconstitution. Discard any unused contents into the appropriate safety container.

Each vial of AlphaNine SD is labeled with the total units expressed as International Units (IU) of Factor IX, which is referenced to the WHO International Standard. One unit approximates the activity in one mL of pooled normal human plasma.

The amount of AlphaNine SD required to establish hemostasis will vary with each patient and depend upon the circumstances. The following formula may be used as a guide in determining the number of units to be administered.^16

In clinical practice there is variability between patients and their clinical response. Therefore, the Factor IX level of each patient should be monitored frequently during replacement therapy.

For pediatric usage: See PRECAUTIONS

Treatment Guidelines for Hemorrhagic Events and Surgery in Patients Diagnosed with Hemophilia B
Type of Hemorrhage or Surgical Procedure | Examples | Treatment Guidelines
Minor Hemorrhages | Bruises, cuts or scrapes, uncomplicated joint hemorrhage | FIX levels should be brought to at least 20-30% (20-30 IU FIX/kg/twice daily) until hemorrhage stops and healing has been achieved (1-2 days).^17,18,19
Moderate Hemorrhages | Nose bleeds, mouth and gum bleeds, dental extractions, hematuria | FIX levels should be brought to 25-50% (25-50 IU FIX/kg/twice daily) until healing has been achieved (2-7 days, on average).^17,18,19,20,21
Major Hemorrhages | Joint and muscle hemorrhages (especially in the large muscles), major trauma, hematuria, intracranial and intraperitoneal bleeding | FIX levels should be brought to 50% for at least 3-5 days (30-50 IU FIX/kg/twice daily). Following this treatment period, FIX levels should be maintained at 20% (20 IU FIX/kg/twice daily) until healing has been achieved. Major hemorrhages may require treatment for up to 10 days.^17,18,19,20,21
Surgery |  | Prior to surgery, FIX should be brought to 50-100% of normal (50-100 IU FIX/kg/twice daily). For the next 7 to 10 days, or until healing has been achieved, the patient should be maintained at 50-100% FIX levels (50-100 IU FIX/kg/twice daily).^17,18,19,20,21

Dosing requirements and frequency of dosing is calculated on the basis of an initial response of 1% FIX increase achieved per IU of FIX infused per kg body weight and an average half-life for FIX of 18 hours. If dosing studies have revealed that a particular patient exhibits a lower response, the dose should be adjusted accordingly.

For pediatric usage: See PRECAUTIONS

RECONSTITUTION

Use Aseptic Technique

1. Warm diluent (Sterile Water for Injection, USP) and concentrate (AlphaNine SD) to at least room temperature (but not above 37 °C).
2. Remove the plastic flip off cap from the diluent vial.
3. Gently swab the exposed stopper surface with a cleansing agent such as alcohol trying to avoid leaving any excess cleansing agent on the stopper.
4. Open the Mix2Vial® package by peeling away the lid (Figure 1). Leave the Mix2Vial in the clear outer packaging.
5. Place the diluent vial upright on an even surface and hold the vial tight and pick up the Mix2Vial in its clear outer packaging. Holding the diluent vial securely, push the blue end of the Mix2Vial vertically down through the diluent vial stopper (Figure 2).
6. While holding onto the diluent vial, carefully remove the clear outer packaging from the Mix2Vial set, ensuring the Mix2Vial remains attached to the diluent vial (Figure 3).
7. Place the product vial upright on an even surface, invert the diluent vial with the Mix2Vial attached.
8. While holding the product vial securely on a flat surface, push the clear end of the Mix2Vial set vertically down through the product vial stopper (Figure 4). The diluent will automatically transfer out of its vial into the product vial. (NOTE: If the Mix2Vial is connected at an angle, the vacuum may be released from the product vial and the diluent will not transfer into the product vial.)
9. With the diluent and product vials still attached to the Mix2Vial, gently swirl the product vial to ensure the product is fully dissolved (Figure 5). Reconstitution requires less than 5 minutes. Do not shake the vial.
10. Disconnect the Mix2Vial into two separate pieces (Figure 6) by holding each vial adapter and twisting counterclockwise. After separating, discard the diluent vial with the blue end of the Mix2Vial.
11. Draw air into an empty, sterile syringe. Keeping the product vial upright with the clear end of the Mix2Vial attached, screw the disposable syringe onto the luer lock portion of the Mix2Vial device by pressing and twisting clockwise. Inject air into the product vial.
12. While keeping the syringe plunger depressed, invert the system upside down and draw the reconstituted product into the syringe by pulling the plunger back slowly (Figure 7).
13. When the reconstituted product has been transferred into the syringe, firmly hold the barrel of the syringe and the clear vial adapter (keeping the syringe plunger facing down) and unscrew the syringe from the Mix2Vial (Figure 8). Hold the syringe upright and push the plunger until no air is left in the syringe. Attach the syringe to a venipuncture set.
14. NOTE: If the same patient is to receive more than one vial of concentrate, the contents of two vials may be drawn into the same syringe through a separate unused Mix2Vial set before attaching to the venipuncture set.
15. Use the prepared drug as soon as possible within three hours after reconstitution.
16. After reconstitution, parenteral drug products should be inspected visually for particulate matter and discoloration prior to administration, whenever solution and container permit. When reconstitution procedure is strictly followed, a few small particles may occasionally remain. The Mix2Vial set will remove particles and the labeled potency will not be reduced.
17. Discard all administration equipment after use into the appropriate safety container. Do not reuse.

HOW SUPPLIED

AlphaNine SD is supplied in sterile, lyophilized form in single dose vials accompanied by 10 mL diluent (Sterile Water for Injection, USP). Factor IX activity, expressed in International Units (IU) which is referenced to WHO International Standard, is stated on the label of each concentrate vial. AlphaNine SD is packaged with a Mix2Vial filter transfer set for use in administration.

It is available in the following potencies, and the product is also color coded based upon assay on the carton and vial label as follows:

Potency | NDC | Assay Color Code
500 IU FIX/10 mL single dose vial | 68516-3610-2 or 68516-3607-2 | 500 IU FIX Range - gray box
1000 IU FIX/10 mL single dose vial | 68516-3611-2 or 68516-3608-2 | 1000 IU FIX Range - green box
1500 IU FIX/10 mL single dose vial | 68516-3612-2 or 68516-3609-2 | 1500 IU FIX Range - blue box

STORAGE

AlphaNine SD is stable for three years, up to the expiration date printed on its label, provided that the storage temperature is between 2 and 8 °C (36 and 46 °F). Do not freeze to prevent damage to diluent vial. May be stored at room temperature not to exceed 30 °C for 1 month. When removed from refrigeration, record the date removed on the space provided on the carton.

Rx only

REFERENCES

1. Plasma Fraction Purification Serial No. 902.155 Patent issued.
2. Data on file at Grifols Biologicals LLC
3. Giles, A.R., Johnston, M., Hoogendoorn, H., Blajchman, M. & Hirsch, J. The Thrombogenicity of Prothrombin Complex Concentrates: I. The Relationship Between In Vitro Characteristics and In Vivo Thrombogenicity in Rabbits. Thromb Res 17:353-366, 1980.
4. Kingdon, H.S., Lundblad, R.L., Veltkamp, J.J. & Aronson, D.L. Potentially Thrombogenic Materials in Factor IX Concentrates. Thromb Diath Haemorrh (Stuttg) 33:617-631, 1975.
5. Prowse, C.V. & Williams, A.E. A Comparison of the In Vitro and In Vivo Thrombogenic Activity of Factor IX Concentrate Using Stasis (Wessler) and Non-Stasis Rabbit Models. Thromb Hemostas 44:81-86, 1980.
6. Wessler, S., Reimer, S.M. & Sheps, M.C. Biologic Assay of a Thrombosis-Inducing Activity in Human Serum. J Appl Physiol 14:943-946, 1959.
7. Herring, S.W. & Heldebrant, C.M. Heat-Treated Pure Factor IX. Proc 5th Int Symp HT, 1986, pp. 151-158.
8. Herring, S.W., Abildgaard, C., Shitanishi, K.T., Harrison, J., Gendler, S. & Heldebrant, C.M. Human Coagulation Factor IX Assessment of Thrombogenicity in Animal Models and Viral Safety. J. Lab. Clin Med. 121: 394-405, 1993.
9. Harrison, J., Abildgaard, C., Lazerson, J., Culbertson, R. & Anderson, G. Assessment of Thrombogenicity of Prothrombin Complex Concentrates in a Porcine Model. Throm Res 38(2): 173-188, 1985.
10. Lee, M., Poon, W., & Kingdon, H. A Two-Phase Linear Regression Model for Biologic Half-Life Data. J Lab Clin Med 115(6): 745-748, 1990.
11. White, G.C., Lundblad, R.L., & Kingdon, H.S. Prothrombin Complex Concentrates: Preparation, Properties, and Clinical Uses. Curr Topic in Hematol 2:203-244, 1979.
12. Goldsmith, J.C., Kasper, C.K., et al. Coagulation Factor IX: Successful Surgical Experience With a Purified Factor IX Concentrate. Amer J Hematol 40: 210-215, 1992.
13. Mannucci, P.M., Bauer, K.A., Gringeri, A., Barzegar, S., Bottasso, B., Simoni L. & Rosenberg, R.D. Thrombin Generation Is Not Increased in the Blood of Hemophilia B Patients After the Infusion of a Purified Factor IX Concentrate. Blood 76(12): 2540-2545, December 15, 1990.
14. Herring, S., Peddada, L., Shitanishi, K., Chavez, D., Chio, A., & Heldebrant, C. Elimination of Virus During Manufacture of a Coagulation Factor IX Concentrate. Abstract presented at XIX International Congress World Federation of Hemophilia, Washington, DC, USA, August 14-19, 1990.
15. Warrier, I., Ewenstein, B.M., Koerper, M.A., Shapiro, A., Key, N., DiMichele, D., Miller, R.T., Pasi, J., Rivard, G.E., Sommer, S.S., Katz, J., Bergmann, F., Ljung, R., Petrini, P., Lusher, J.M. Journal of Pediatric Hematology/Oncology 19(1):23-27, 1997.
16. Zauber, N.P. & Levine, J. Factor IX Levels in Patients with Hemophilia B (Christmas Disease) Following Transfusion with Concentrates of Factor IX or Fresh Frozen Plasma (FFP). Medicine 56:213-224, 1977.
17. Nillson, I.M.: Hemorrhagic and Thrombotic Diseases: London, John Wiley and Sons, 1974.
18. Roberts, H.R. and Eberst, M.E.: Current Management of Hemophilia B. Hematology/Oncology Clinics of North America 7(6): 1269-1280, 1993.
19. Roberts, H.R. and Gray, T.F.: Clinical Aspects of Hemophilia B. In Hematology: Basic Principles and Practice, 2nd Edition, pp 1678-1685, Churchill Livingston.
20. Hedner, U. and Davie, E.W.: In “Hemostasis and Thrombosis: Basic Principles and Clinical Practice”, eds. Colman, R.W., Hirsh, J., Marder, V.J., Salzman, E.W., 2nd Edition, Philadelphia, J.B. Lippincot Co, 1987.
21. Levin, P.H.: In “Hemostasis and Thrombosis: Basic Principles and Clinical Practice”, eds. Colman, R.W., Hirsh, J., Marder, V.J., Salzman, E.W., 2nd Edition, Philadelphia, J.B, Lippincot Co, 1987.

Manufactured by:
Grifols Biologicals LLC
5555 Valley Boulevard
Los Angeles, CA 90032, U.S.A.
U.S. License No. 1694
DATE OF REVISION: November 2022

3063702

Principal Display Panel – 500 IU Vial Label
NDC 68516-3604-2 500 IU FIX Range
Coagulation Factor IX (Human)
AlphaNine® SD
Solvent Detergent Treated / Virus
Filtered
Storage: Store between 2 and 8 °C.
May be stored at room temperature
not to exceed 30 °C for 1 month.
Rx Only. Single dose container for
intravenous administration only.
U.S. License No. 1694 10 mL
Instructions: Reconstitute with 10 mL
Sterile Water for Injection, USP.
Administer promptly after
reconstitution and do not refrigerate.
Discard unused contents. For
information on dosage and
directions for administration, see
accompanying pamphlet. Contains
no preservatives. The patient and
physician should discuss the risks
and benefits of this product.
Grifols Biologicals LLC
5555 Valley Boulevard,
Los Angeles, CA 90032, U.S.A.
Lot
EXP
IU FIX/Vial 3063701
Lot
IU FIX/Vial
Alphanine® SD
10 mL NDC 68516-3604-2

Principal Display Panel – 1000 IU Vial Label
NDC 68516-3605-2 1000 IU FIX Range
Coagulation Factor IX (Human)
AlphaNine® SD
Solvent Detergent Treated / Virus
Filtered
Storage: Store between 2 and 8 °C.
May be stored at room temperature
not to exceed 30 °C for 1 month.
Rx Only. Single dose container for
intravenous administration only.
U.S. License No. 1694 10 mL
Instructions: Reconstitute with 10 mL
Sterile Water for Injection, USP.
Administer promptly after
reconstitution and do not refrigerate.
Discard unused contents. For
information on dosage and
directions for administration, see
accompanying pamphlet. Contains
no preservatives. The patient and
physician should discuss the risks
and benefits of this product.
Grifols Biologicals LLC
5555 Valley Boulevard,
Los Angeles, CA 90032, U.S.A.
Lot
EXP
IU FIX/Vial 3063699
Lot
IU FIX/Vial
Alphanine® SD
10 mL NDC 68516-3605-2

Principal Display Panel – 1500 IU Vial Label
NDC 68516-3606-2 1500 IU FIX Range
Coagulation Factor IX (Human)
AlphaNine® SD
Solvent Detergent Treated / Virus
Filtered
Storage: Store between 2 and 8 °C.
May be stored at room temperature
not to exceed 30 °C for 1 month.
Rx Only. Single dose container for
intravenous administration only.
U.S. License No. 1694 10 mL
Instructions: Reconstitute with 10 mL
Sterile Water for Injection, USP.
Administer promptly after
reconstitution and do not refrigerate.
Discard unused contents. For
information on dosage and
directions for administration, see
accompanying pamphlet. Contains
no preservatives. The patient and
physician should discuss the risks
and benefits of this product.
Grifols Biologicals LLC
5555 Valley Boulevard,
Los Angeles, CA 90032, U.S.A.
Lot
EXP
IU FIX/Vial 3063697
Lot
IU FIX/Vial
Alphanine® SD
10 mL NDC 68516-3606-2

Principal Display Panel – 500 IU Carton Label
NDC 68516-3610-2 500 IU FIX Range
Coagulation Factor IX (Human)
AlphaNine® SD
Solvent Detergent Treated / Virus Filtered
Rx only
For Intravenous Administration 10 mL
GRIFOLS

Contents:
One vial Coagulation Factor IX (Human), AlphaNine®
SD, one vial 10 mL Sterile Water for Injection, USP,
one Mix2Vial® filter transfer set, and directions for
use.
For intravenous administration.
The reconstituted product contains not more than
0.04 unit of heparin, and not more than 0.2 mg of
dextrose, and not more than 1.0 µg polysorbate 80
and 0.10 µg tri(n-butyl) phosphate per IU of Factor IX.
Contains no preservatives.
Administer within three hours of reconstitution.
Discard unused contents.
GRIFOLS
Warning: This product is prepared from large
pools of human plasma. Human blood and its
components may transmit infectious agents. See
package insert, WARNINGS AND PRECAUTIONS.
Instructions: The patient and physician should
discuss the risks and benefits of this product.
For information on dosage and directions for
administration, see enclosed package insert.
Storage: Store between 2 and 8 °C. Avoid
freezing which might damage diluent bottle.
May be stored at room temperature not to exceed
30 °C for 1 month.
Single dose container for intravenous
administration only.
Date removed from refrigeration:
Grifols Biologicals LLC
5555 Valley Boulevard
Los Angeles, CA 90032, U.S.A.
U.S. License No 1694
GRIFOLS
GTIN 00368516361023
LOT XXXXXXXXXX
EXP DDMMMYYYY
SN XXXXXXXXXX XXXXXX
IU FI X/Vial XXXX
3063700

Principal Display Panel – 1000 IU Carton Label
NDC 68516-3611-2 1000 IU FIX Range
Coagulation Factor IX (Human)
AlphaNine® SD
Solvent Detergent Treated / Virus Filtered
Rx only
For Intravenous Administration 10 mL
GRIFOLS

Contents:
One vial Coagulation Factor IX (Human), AlphaNine®
SD, one vial 10 mL Sterile Water for Injection, USP,
one Mix2Vial® filter transfer set, and directions for
use.
For intravenous administration.
The reconstituted product contains not more than
0.04 unit of heparin, and not more than 0.2 mg of
dextrose, and not more than 1.0 µg polysorbate 80
and 0.10 µg tri(n-butyl) phosphate per IU of Factor IX.
Contains no preservatives.
Administer within three hours of reconstitution.
Discard unused contents.
Warning: This product is prepared from large
pools of human plasma. Human blood and its
components may transmit infectious agents. See
package insert, WARNINGS AND PRECAUTIONS.
Instructions: The patient and physician should
discuss the risks and benefits of this product.
For information on dosage and directions for
administration, see enclosed package insert.
Storage: Store between 2 and 8 °C. Avoid
freezing which might damage diluent bottle.
May be stored at room temperature not to exceed
30 °C for 1 month.
Single dose container for intravenous
administration only.
Date removed from refrigeration:
Grifols Biologicals LLC
5555 Valley Boulevard
Los Angeles, CA 90032, U.S.A.
U.S. License No 1694
GRIFOLS
GTIN 00368516361122
LOT XXXXXXXXXX
EXP DDMMMYYYY
SN XXXXXXXXXX XXXXXX
IU FI X/Vial XXXX
3063698

Principal Display Panel – 1500 IU Carton Label
NDC 68516-3612-2 1500 IU FIX Range
Coagulation Factor IX (Human)
AlphaNine® SD
Solvent Detergent Treated / Virus Filtered
Rx only
For Intravenous Administration 10 mL
GRIFOLS

Contents:
One vial Coagulation Factor IX (Human), AlphaNine®
SD,one vial 10 mL Sterile Water for Injection, USP,
one Mix2Vial® filter transfer set, and directions for
use.
For intravenous administration.
The reconstituted product contains not more than
0.04 unit of heparin, and not more than 0.2 mg of
dextrose, and not more than 1.0 µg polysorbate 80
and 0.10 µg tri(n-butyl) phosphate per IU of Factor IX.
Contains no preservatives.
Administer within three hours of reconstitution.
Discard unused contents.
GRIFOLS
Warning: This product is prepared from large
pools of human plasma. Human blood and its
components may transmit infectious agents. See
package insert, WARNINGS AND PRECAUTIONS.
Instructions: The patient and physician should
discuss the risks and benefits of this product.
For information on dosage and directions for
administration, see enclosed package insert.
Storage: Store between 2 and 8 °C. Avoid
freezing which might damage diluent bottle.
May be stored at room temperature not to exceed
30 °C for 1 month.
Single dose container for intravenous
administration only.
Date removed from refrigeration:
Grifols Biologicals LLC
5555 Valley Boulevard
Los Angeles, CA 90032, U.S.A.
U.S. License No 1694
GRIFOLS
GTIN 00368516361221
LOT XXXXXXXXXX
EXP DDMMMYYYY
SN XXXXXXXXXX XXXXXX
IU FI X/Vial XXXX
3063696

NDC 76297-002-12
Sterile Water for Injection, USP
10 mL
Rx Only
For reconstitution of accompanying product
Single-Dose Container, Nonpyrogenic
Do not use unless clear. No antimicrobial agent or other substance has been added. Do not use for intravascular injection without making approximately isotonic by addition of suitable solute. Discard unused portion.
Mfd by: Laboratorios Grifols, S. A. Parets del Vallès,
Barcelona 08150 Spain
Lot
EXP
3057423